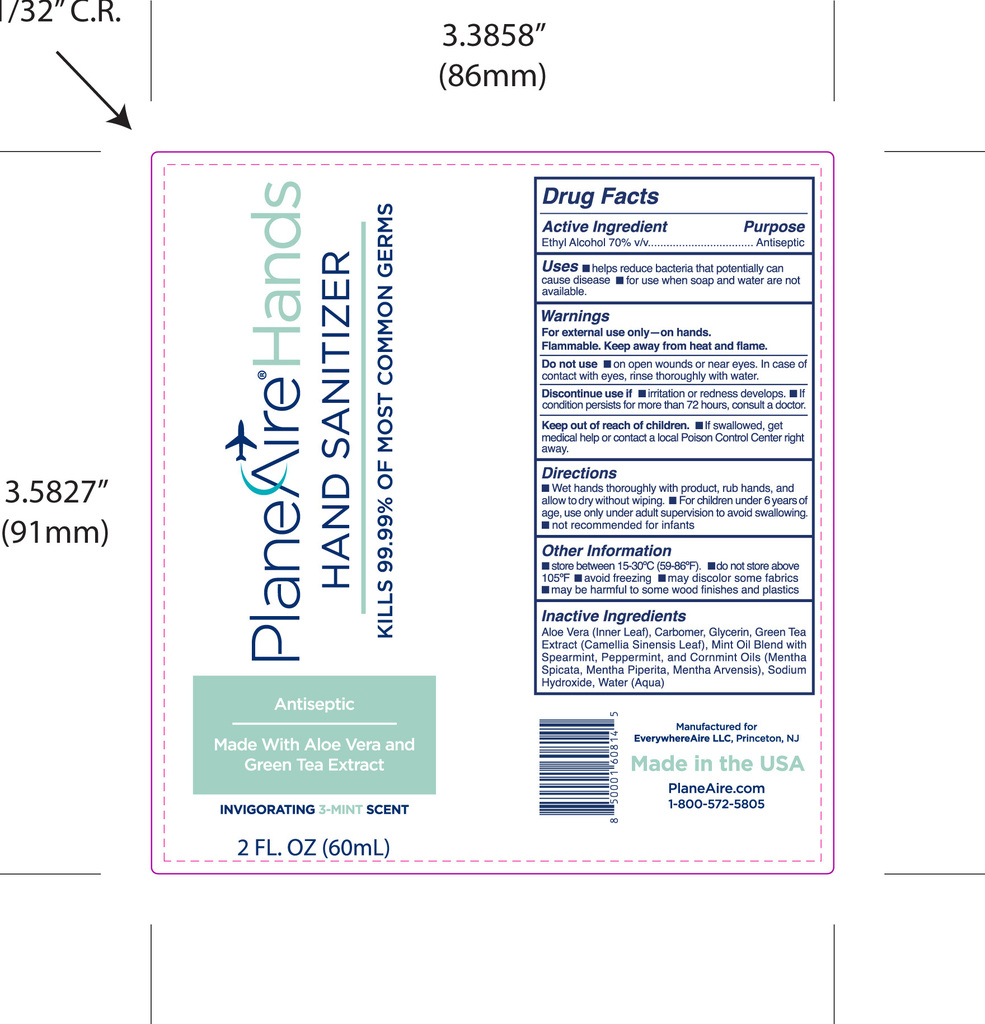 DRUG LABEL: PlaneAire Hands
NDC: 80335-112 | Form: GEL
Manufacturer: EverywhereAire LLC
Category: otc | Type: HUMAN OTC DRUG LABEL
Date: 20231220

ACTIVE INGREDIENTS: ALCOHOL 70 mL/100 mL
INACTIVE INGREDIENTS: GREEN TEA LEAF; PEPPERMINT OIL; SODIUM HYDROXIDE; ALOE VERA LEAF POLYSACCHARIDES; SPEARMINT; MINT; GLYCERIN; WATER

Plane Aire Hands gel Cool Mint aloe green tea

Active Ingredient(s)

Ethyl Alcohol 70% v/v

Purpose

Antiseptic,

Use

Hand Sanitizer to help reduce bacteria that potentially can cause disease. For use when soap and water are not available.

Warnings

For external use only on hands. Flammable. Keep away from heat and flame

Do not use

- on open skin wounds or near eyes. In case of contact with eyes, rinse thoroughly with water.

When using this product keep out of eyes. In case of contact with eyes, rinse eyes thoroughly with water.
Stop use if irritation or rash occurs. If condition persists for more than 72 hours, consult a doctor.
Keep out of reach of children. If swallowed, get medical help or contact a Poison Control Center right away.

Stop use and ask a doctor if irritation or rash occurs. These may be signs of a serious condition.

Keep out of reach of children. If swallowed, get medical help or contact a Poison Control Center right away.

Directions

Wet hands thoroughly with product, rub hands, and allow to dry without wiping.

For children under 6 years of age, use only under adult supervision to avoid swallowing

not recommended for infants

Directions

Wet hands thoroughly with product, rub hands, and allow to dry without wiping.

For children under 6 years of age, use only under adult supervision to avoid swallowing

not recommended for infants

Other information

- Store between 15-30C (59-86F)
- do not store above 105F
- avoid freezing
- may discolor some fabrics
- may be harmful to some wood finishes and plastics

Inactive ingredients

aloe vera inner leaf, carbomer, glycerin, green tea extract, mint oil fragrance blend , sodium hydroxide, water

Package Label - Principal Display Panel

60 mL NDC: 80335-112-02